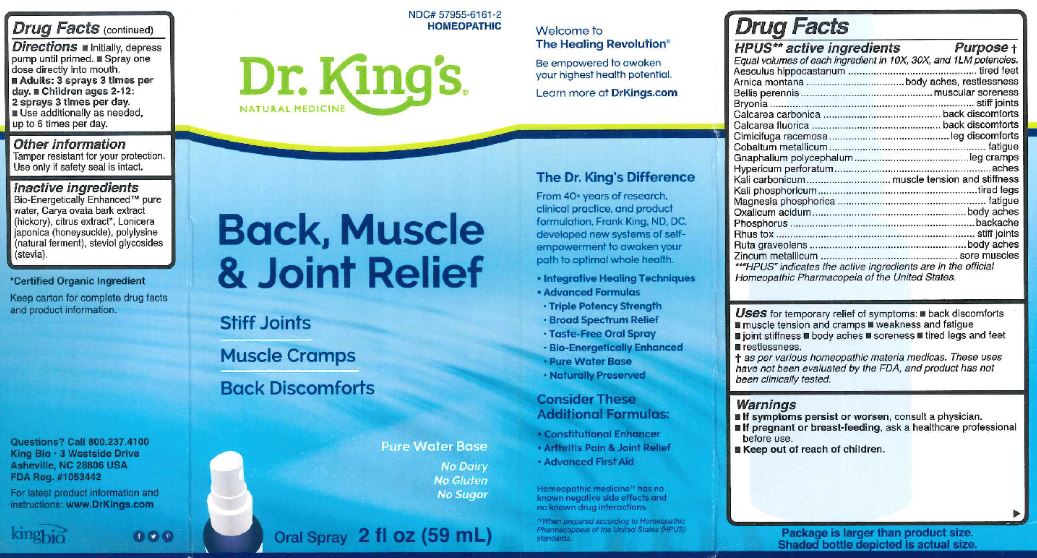 DRUG LABEL: Back Muscle and Joint Relief
NDC: 57955-6161 | Form: LIQUID
Manufacturer: King Bio Inc.
Category: homeopathic | Type: HUMAN OTC DRUG LABEL
Date: 20180410

ACTIVE INGREDIENTS: HORSE CHESTNUT 10 [hp_X]/59 mL; ARNICA MONTANA 10 [hp_X]/59 mL; BELLIS PERENNIS 10 [hp_X]/59 mL; BRYONIA ALBA ROOT 10 [hp_X]/59 mL; OYSTER SHELL CALCIUM CARBONATE, CRUDE 10 [hp_X]/59 mL; CALCIUM FLUORIDE 10 [hp_X]/59 mL; BLACK COHOSH 10 [hp_X]/59 mL; COBALT 10 [hp_X]/59 mL; PSEUDOGNAPHALIUM OBTUSIFOLIUM 10 [hp_X]/59 mL; HYPERICUM PERFORATUM 10 [hp_X]/59 mL; POTASSIUM CARBONATE 10 [hp_X]/59 mL; POTASSIUM PHOSPHATE, DIBASIC 10 [hp_X]/59 mL; MAGNESIUM PHOSPHATE, DIBASIC TRIHYDRATE 10 [hp_X]/59 mL; OXALIC ACID 10 [hp_X]/59 mL; PHOSPHORUS 10 [hp_X]/59 mL; TOXICODENDRON PUBESCENS LEAF 10 [hp_X]/59 mL; RUTA GRAVEOLENS FLOWERING TOP 10 [hp_X]/59 mL; ZINC 10 [hp_X]/59 mL
INACTIVE INGREDIENTS: WATER; CARYA OVATA BARK; CITRUS BIOFLAVONOIDS; LONICERA JAPONICA FLOWER; POLYEPSILON-LYSINE (4000 MW); REBAUDIOSIDE A

Back, Muscle and Joint Relief

HPUS Active Ingredients

Equal volumes of each ingredient in 10X, 30X and 1LM potencies.

Aesculus hippocastanum

Arnica montana

Bellis perennis

Bryonia

Calcarea carbonica

Calcarea fluorica

Cimicifuga racemosa

Cobaltum metallicum

Gnaphalium polycephalum

Hypericum perforatum

Kali carbonicum

Kali Phosphoricum

Magnesia phosphorica

Oxalicum acidum

Phosphorus

Rhus tox

Ruta graveolens

Zincum metallicum

Inactive Ingredients

Bio-Energetically Enhanced pure water, Carya ovata bark extract (hickory), citrus extract, Lonicera japonica (honeysuckle), polylysine (natural ferment), steviol glycosides (stevia).

Purpose

HPUS active ingredients Purpose

Equal volumes of each ingredient in 10X, 30X and 1LM potencies.

Aesculus hippocastanum...................................................tired feet

Arnica montana.................................................................body aches, restlessness

Bellis perennis...................................................................muscular soreness

Bryonia.............................................................................stiff joints

Calcarea carbonica............................................................back discomforts

Calcarea fluorica................................................................back discomforts

Cimicifuga racemosa..........................................................leg discomforts

Cobaltum metallicum...........................................................fatigue

Gnaphalium polycephalum..................................................leg cramps

Hypericum perforatum........................................................aches

Kali carbonicum..................................................................muscle tension and stiffness

Kali Phosphoricum..............................................................tired legs

Magnesia phosphorica........................................................fatigue

Oxalicum acidum................................................................body aches

Phosphorus........................................................................backache

Rhus toxicodendron............................................................stiff joints

Ruta graveolens.................................................................body aches

Zincum metallicum.............................................................sore muscles

Directions

Initially, depress pump until primed.

Spray one dose directly into mouth.

Adults: 3 sprays 3 times per day.

Children ages 2 - 12: 2 sprays 3 times per day.

Use additionally as needed up to 6 times per day.

Warnings

Warning: If symptoms persist or worsen, consult a physician.

If pregnant or breast-feeding, ask a healthcare professional before use.

Keep out of reach of children.

Other Information

Tamper resistant for your protection. Use only if safety seal is intact.

Uses

for temporary relief of symptoms:

- back discomforts
- muscle tension and cramps
- weakness and fatigue
- joint stiffness
- body aches
- soreness
- tired legs and feet
- restlessness